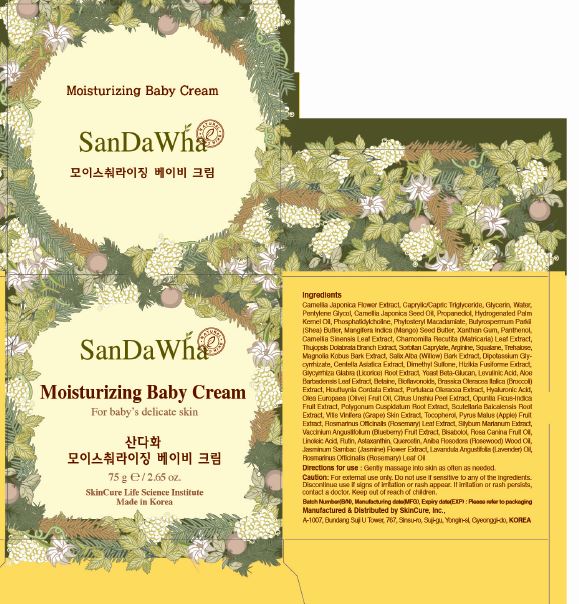 DRUG LABEL: Sandawha Moisturizing Baby
NDC: 72289-0006 | Form: CREAM
Manufacturer: SKINCURE INC
Category: otc | Type: HUMAN OTC DRUG LABEL
Date: 20190224

ACTIVE INGREDIENTS: GLYCERIN 3.1545 g/100 g
INACTIVE INGREDIENTS: PANTHENOL; SQUALENE; WATER

Drug Facts

ACTIVE INGREDIENT

glycerin

INACTIVE INGREDIENT

Camellia Japonica Flower Extract
Caprylic/Capric Triglyceride
Glycerin
Water(Aqua)
Pentylene Glycol
Camellia Japonica Seed Oil
Propanediol
Hydrogenated Palm Kernel Oil
Phosphatidylcholine
Phytosteryl Macadamiate
Butyrospermum Parkii (Shea) Butter
Mangifera Indica (Mango) Seed Butter
Xanthan Gum
Panthenol
Camellia Sinensis Leaf Extract
Chamomilla Recutita (Matricaria) Leaf Extract
Thujopsis Dolabrata Branch Extract
Sorbitan Caprylate
Arginine
Squalane
Trehalose
Magnolia Kobus Bark Extract
Salix Alba (Willow) Bark Extract
Dipotassium Glycyrrhizate
Centella Asiatica Extract
Dimethyl Sulfone
Hizikia Fusiforme Extract
Glycyrrhiza Glabra (Licorice) Root Extract
Yeast Beta-Glucan
Levulinic Acid
Betaine
Houttuynia Cordata Extract
Portulaca Oleracea Extract
Hyaluronic Acid
Aloe Barbadensis Leaf Extract
Olea Europaea (Olive) Fruit Oil
Citrus Unshiu Peel Extract
Opuntia Ficus-Indica Fruit Extract
Polygonum Cuspidatum Root Extract
Scutellaria Baicalensis Root Extract
Vitis Vinifera (Grape) Skin Extract
Tocopherol
Pyrus Malus (Apple) Fruit Extract
Rosmarinus Officinalis (Rosemary) Leaf Extract
Silybum Marianum Extract
Vaccinium Angustifolium (Blueberry) Fruit Extract
Bioflavonoids
Bisabolol
Rosa Canina Fruit Oil
Brassica Oleracea Italica (Broccoli) Extract
Linoleic Acid
Rutin
Astaxanthin
Quercetin
Aniba Rosodora (Rosewood) Wood Oil
Jasminum Sambac (Jasmine) Flower Extract
Lavandula Angustifolia (Lavender) Oil
Rosmarinus Officinalis (Rosemary) Leaf Oil

PURPOSE

suitable for delicate baby's skin

soothes and protects sensitive skin

keep out of reach of the children

INDICATIONS AND USAGE

Gently massage into skin as often as needed

WARNINGS

for external use only

do not use if sensitive to any of the ingredients

discontinue use if signs of irritation or rash appear

if irritation or rash persists, contact a doctor

DOSAGE AND ADMINISTRATION

for external use only